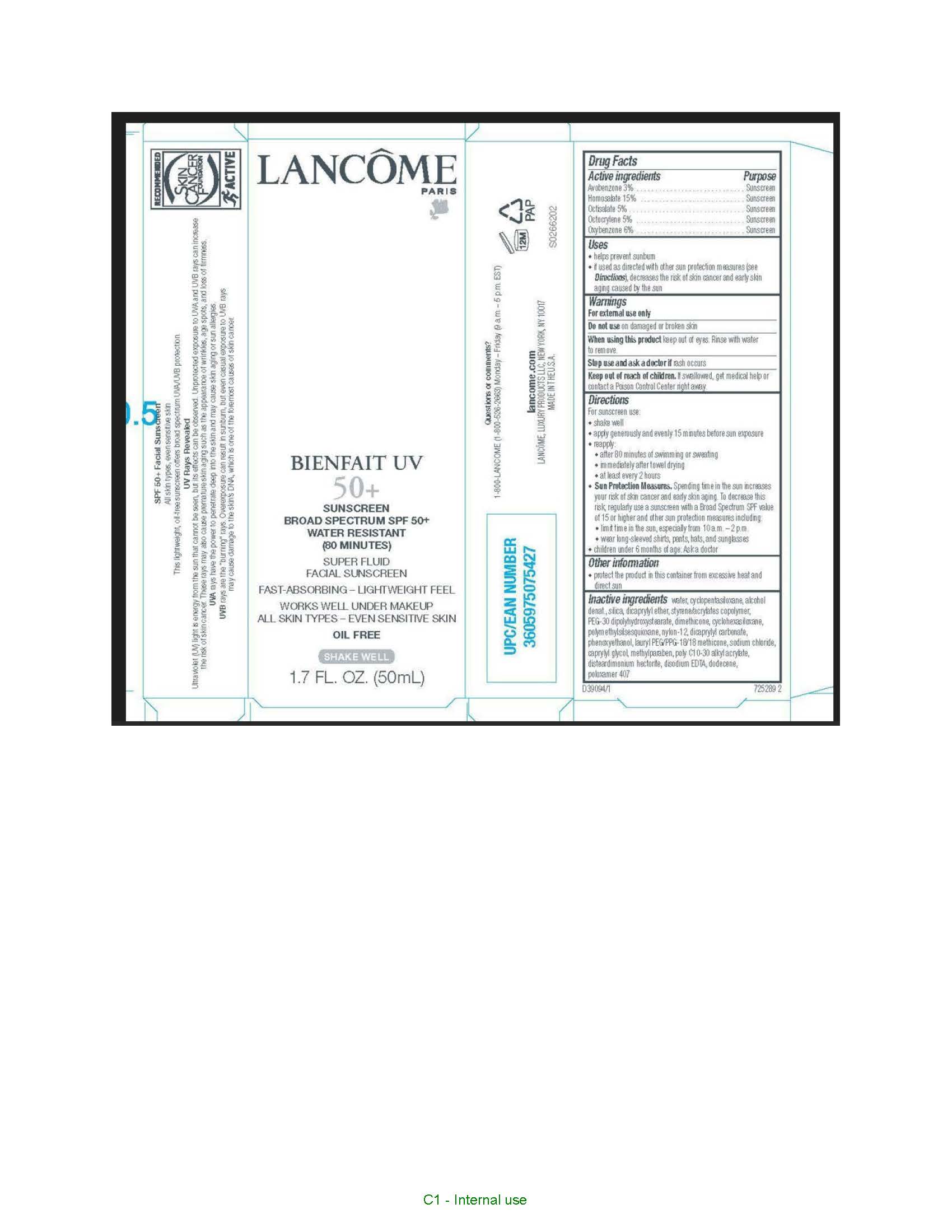 DRUG LABEL: Lancome Paris Bienfait UV 50 Plus Broad Spectrum SPF 50 Plus Water Resistant 80 Minutes Super Fluid Facial Sunscreen
NDC: 49967-754 | Form: LOTION
Manufacturer: L'Oreal USA Products Inc
Category: otc | Type: HUMAN OTC DRUG LABEL
Date: 20240115

ACTIVE INGREDIENTS: AVOBENZONE 30 mg/1 mL; HOMOSALATE 150 mg/1 mL; OCTISALATE 50 mg/1 mL; OCTOCRYLENE 50 mg/1 mL; OXYBENZONE 60 mg/1 mL
INACTIVE INGREDIENTS: WATER; ALCOHOL; NYLON-12; POLOXAMER 407

Drug Facts

Active ingredients

Avobenzone 3%

Homosalate 15%

Octisalate 5%

Octocrylene 5%

Oxybenzone 6%

Purpose

Sunscreen

Uses

- helps prevent sunburn
- if used as directed with other sun protection measures (see Directions), decreases the risk of skin cancer and early skin aging caused by the sun

Warnings

For external use only

Do not use

on damaged or broken skin

When using this product

keep out of eyes. Rinse with water to remove.

Stop use and ask a doctor if

rash occurs

Keep out of reach of children.

If swallowed, get medical help or contact a Poison Control Center right away.

Directions

For sunscreen use:

● shake well

● apply generously and evenly 15 minutes before sun exposure

● reapply:

● after 80 minutes of swimming or sweating

● immediately after towel drying

● at least every 2 hours

● Sun Protection Measures. Spending time in the sun increases your risk of skin cancer and early skin aging. To decrease this risk, regularly use a sunscreen with a Broad Spectrum SPF value of 15 or higher and other sun protection measures including:

● limit time in the sun, especially from 10 a.m. – 2 p.m.

● wear long-sleeved shirts, pants, hats, and sunglasses

● children under 6 months of age: Ask a doctor

Other information

protect the product in this container from excessive heat and direct sun

Inactive ingredients

water, cyclopentasiloxane, alcohol denat., silica, dicaprylyl ether, styrene/acrylates copolymer, PEG-30 dipolyhydroxystearate, dimethicone, cyclohexasiloxane, polymethylsilsesquioxane, nylon-12, dicaprylyl carbonate, phenoxyethanol, lauryl PEG/PPG-18/18 methicone, sodium chloride, capryly glycol, methylparaben, poly C10-30 alkyl acrylate, disteardimonium hectorite, disodium EDTA, dodecene, poloxamer 407

Questions or comments?

1-800-LANCOME (1-800-526-2663) Monday - Friday (9 a.m. - 5 p.m. EST)